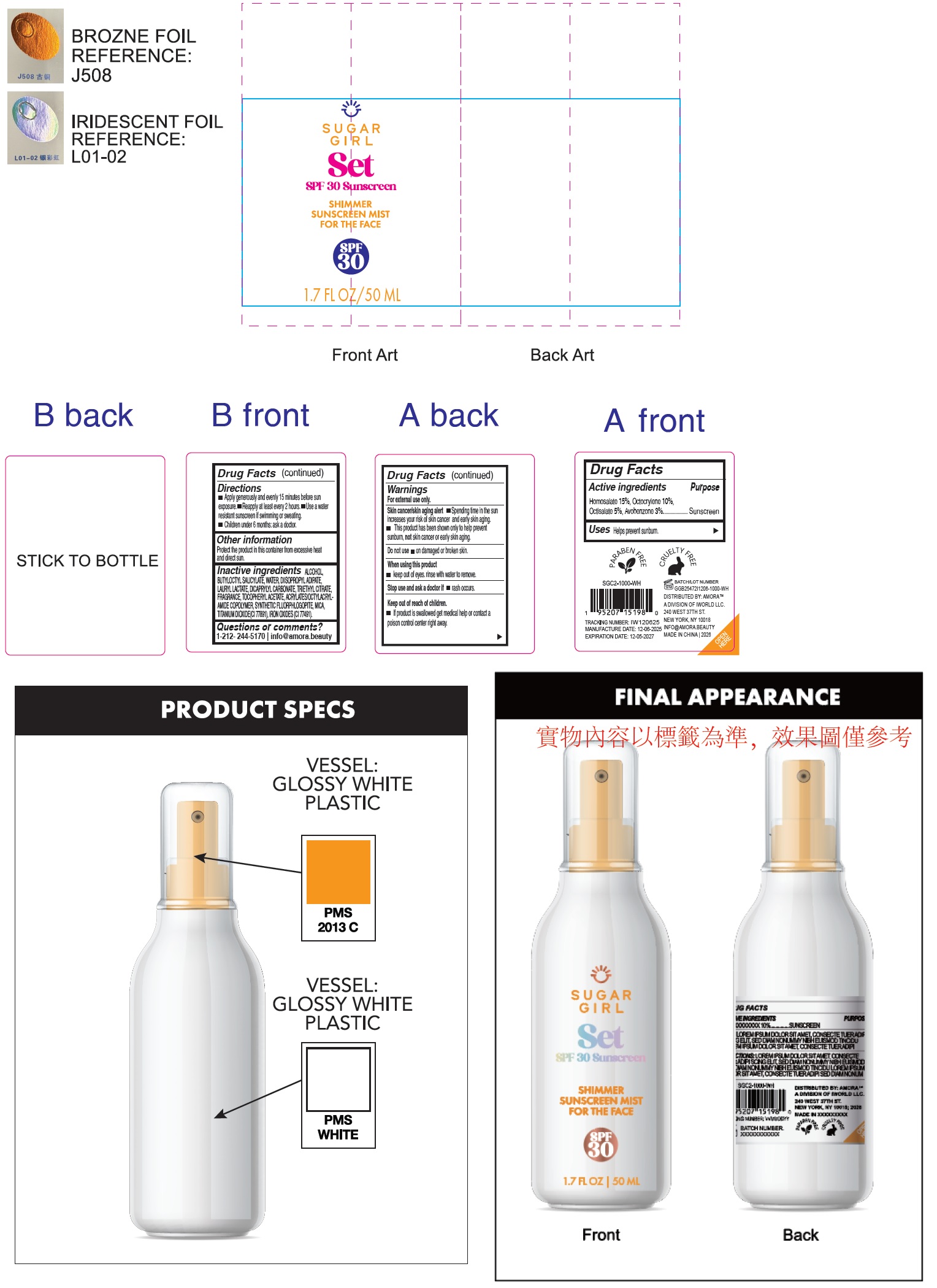 DRUG LABEL: Sugargirl Set SPF 30 Sunscreen Shimmer Sunscreen Mist For the Face
NDC: 85179-043 | Form: LIQUID
Manufacturer: I World LLC
Category: otc | Type: HUMAN OTC DRUG LABEL
Date: 20260127

ACTIVE INGREDIENTS: HOMOSALATE 150 mg/1 mL; OCTOCRYLENE 100 mg/1 mL; OCTISALATE 50 mg/1 mL; AVOBENZONE 30 mg/1 mL
INACTIVE INGREDIENTS: ALCOHOL; BUTYLOCTYL SALICYLATE; WATER; DIISOPROPYL ADIPATE; LAURYL LACTATE; DICAPRYLYL CARBONATE; TRIETHYL CITRATE; .ALPHA.-TOCOPHEROL ACETATE; ACRYLATE/ISOBUTYL METHACRYLATE/N-TERT-OCTYLACRYLAMIDE COPOLYMER (40000 MW); MICA; TITANIUM DIOXIDE; FERRIC OXIDE RED

Sugargirl Set SPF 30 Sunscreen Shimmer Sunscreen Mist For the Face

Active ingredients

Homosalate 15%, Octocrylene 10%, Octisalate 5%, Avobenzone 3%

Purpose

Sunscreen

Uses

- Helps prevent sunburn.

Warnings

For external use only.
Skin cancer/skin aging alert

- Spending time in the sun increases your risk of skin cancer and early skin aging.
- This product has been shown only to help prevent sunburn, not skin cancer or early skin aging.

Do not use

- on damaged or broken skin.

when using this product

- keep out of eyes. rinse with water to remove.

Stop use and ask a doctor if

- rash occurs.

Keep out of reach of children.

- If product is swallowed get medical help or contact a poison control centre right away.

Directions

- Apply generously and evenly 15 minutes before sun exposer.
- Reapply at least every 2 hours.
- Use a water resistant sunscreen if swimming or sweating.
- Children under 6 month: ask a doctor.

Other information

Protect the product in this container from excessive heat and direct sun.

Inactive ingredients

ALCOHOL, BUTYLOCTYL SALICYLATE, WATER, DIISOPROPYL ADIPATE, LAURYL LACTATE, DICAPRYLYL CARBONATE, TRIETHYL CITRATE, FRAGRANCE, TOCOPHERYL ACETATE, ACRYLATES/OCTYLACRYLAMIDE COPOLYMER, SYNTHETIC FLUORPHLOGOPITE, MICA, TITANIUM DIOXIDE(CI 77891), IRON OXIDES (CI 77491).

Questions or comments?

1-212-244-5170 info@amora.beauty